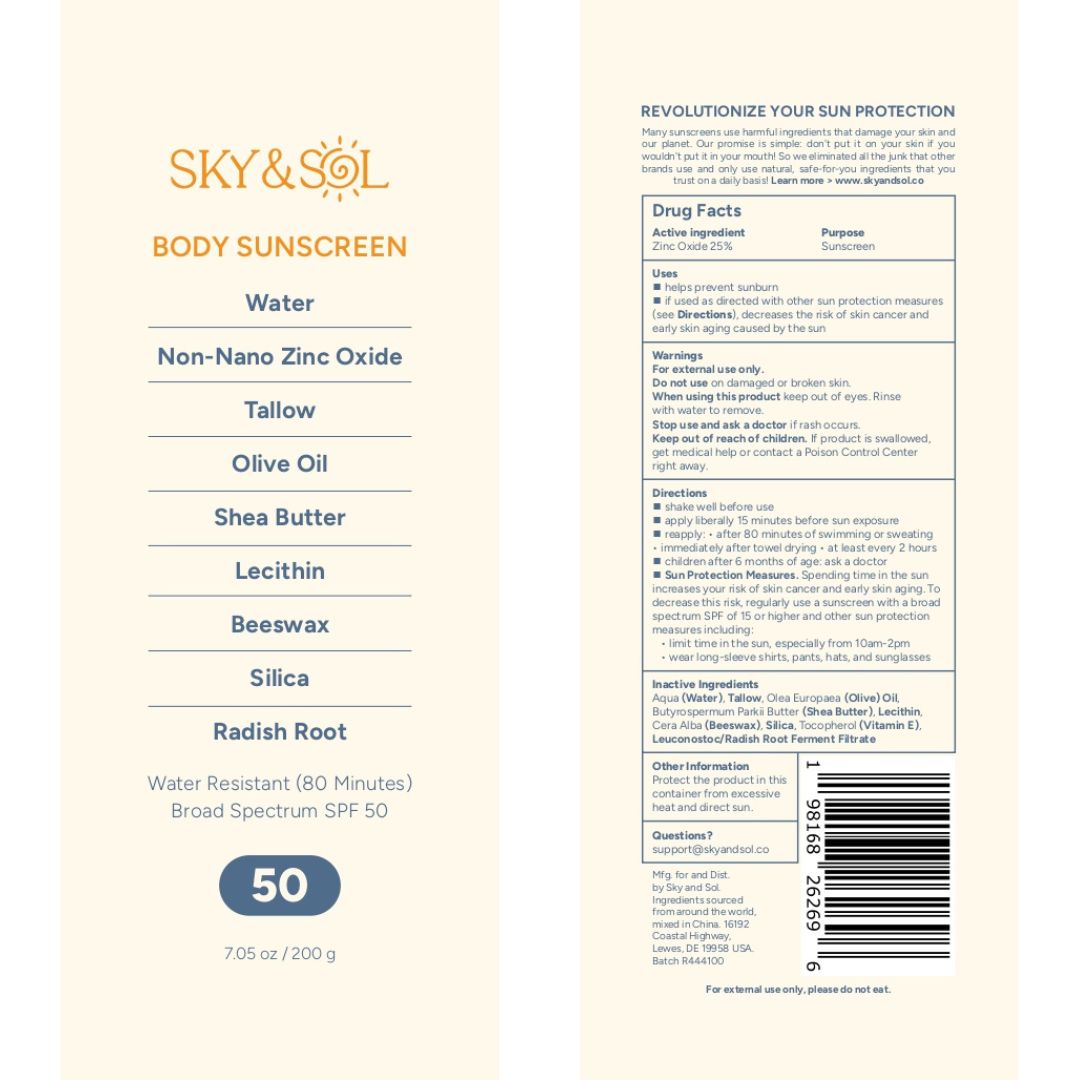 DRUG LABEL: Sky and Sol Body Sunscreen
NDC: 84632-0050 | Form: CREAM
Manufacturer: Delta Ecommerce LLC
Category: otc | Type: HUMAN OTC DRUG LABEL
Date: 20251121

ACTIVE INGREDIENTS: ZINC OXIDE 25 g/100 g
INACTIVE INGREDIENTS: LEUCONOSTOC/RADISH ROOT FERMENT FILTRATE; WATER; TALLOW; LIMONIA ACIDISSIMA BARK; BEESWAX; LECITHIN, SUNFLOWER; BABASSU OIL

Sky and Sol Body Sunscreen

PURPOSE

Sunscreen

INDICATIONS AND USAGE

helps prevent sunburn; if used as directed with other sun protection measures (see Directions), decreases the risk of skin cancer and early skin aging caused by the sun

DOSAGE AND ADMINISTRATION

◼ shake well before use
◼ apply liberally 15 minutes before sun exposure
◼ reapply: • after 80 minutes of swimming or sweating
• immediately after towel drying • at least every 2 hours

WARNINGS

For external use only.
Do not use on damaged or broken skin.
When using this product keep out of eyes. Rinse
with water to remove.
Stop use and ask a doctor if rash occurs.

Keep Out of Reach of Children: Keep out of reach of children. If swallowed, get medical help or contact a Poison Control Center right away.

INACTIVE INGREDIENT

Tallow, Olea Europaea Oil, Cera Alba, Butyrospermum Parkii Butter, Simmondsia Chinensis Ester, Propolis